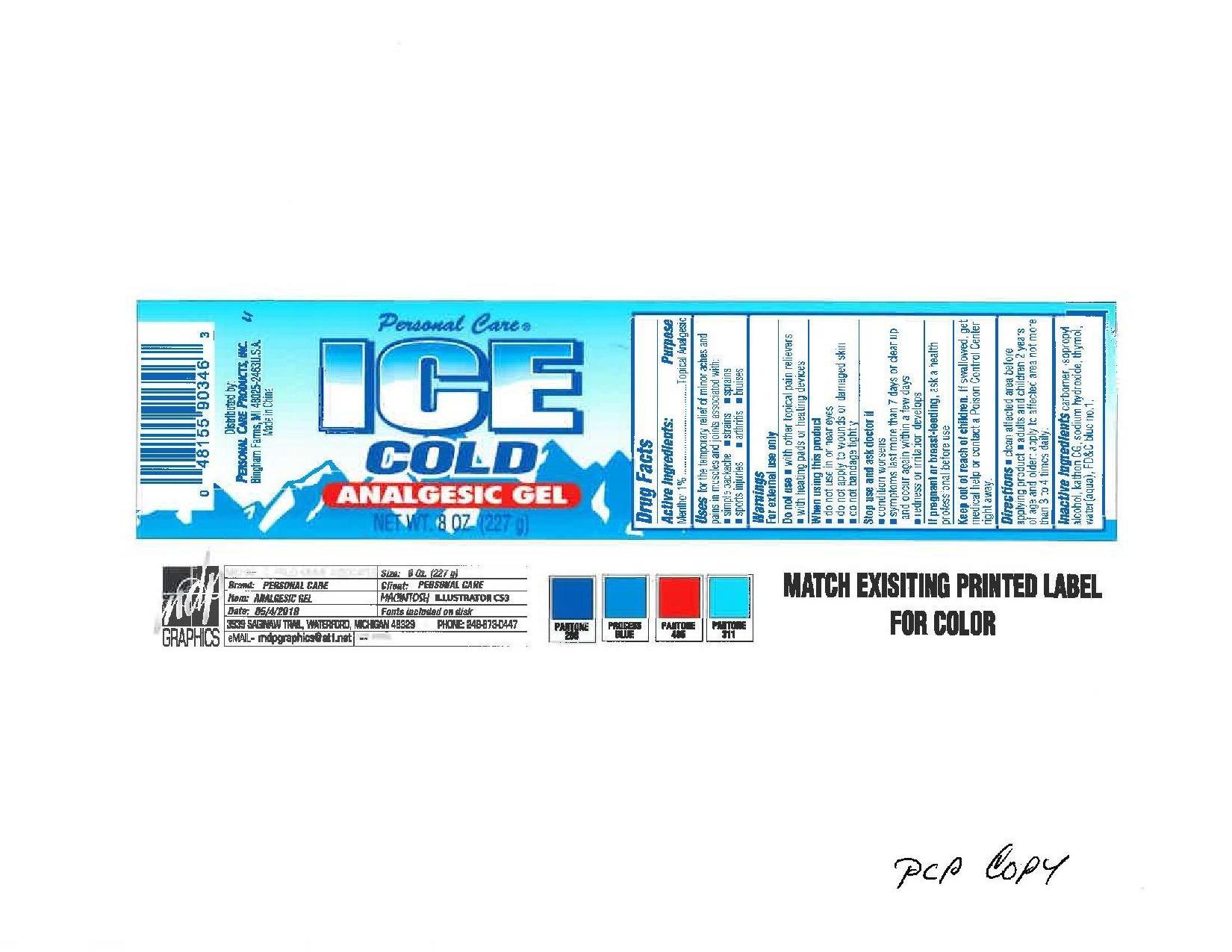 DRUG LABEL: Ice Cold Analgesic
NDC: 29500-9034 | Form: GEL
Manufacturer: Personal Care Products
Category: otc | Type: HUMAN OTC DRUG LABEL
Date: 20110826

ACTIVE INGREDIENTS: MENTHOL 2.27 g/227 g
INACTIVE INGREDIENTS: ISOPROPYL ALCOHOL; SODIUM HYDROXIDE; THYMOL; WATER; FD&C BLUE NO. 1

Ice Cold analgesic

Active Ingredients:

Menthol 1%

Purpose

Topical analgesic

Keep out of reach of children. If swallowed get medical help or contact a poison control center right away.

INDICATIONS AND USAGE

Uses for the temporary relief of minor aches and pains in muscles and joints associated with:
simple backache

sports injuries

strains

arthritis

sprains

bruises

Warnings
For external use only
Do not use with other topical pain relievers, with heating pads or heating devices
When using this product do not use in or near eyes, do not apply to wounds or damaged skin
do not bandage tightly
Stop use and ask doctor if condition worsens, symptoms last more than days or clear up and occur again within a few days, redness or irritation develops
If pregnant or breast feeding ask a health professional before use.

Directions

Clean affected area before applying product

adults and children 2 years of age and older; apply to affected area not more than 3-4 times daily

INACTIVE INGREDIENT

Inactive ingredients carbomer, isopropyl alcohol, kathon CG, sodium hydroxide, thymol, water (aqua), FD and C blue no.1

PACKAGE LABEL

Personal Care

Ice cold

analgesic gel

New wt. 8 oz. (227 g)